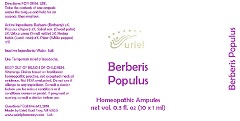 DRUG LABEL: Berberis Populus
NDC: 48951-2131 | Form: LIQUID
Manufacturer: Uriel Pharmacy Inc.
Category: homeopathic | Type: HUMAN OTC DRUG LABEL
Date: 20181210

ACTIVE INGREDIENTS: BERBERIS VULGARIS ROOT BARK 2 [hp_X]/1 mL; LARIX DECIDUA RESIN 8 [hp_X]/1 mL; WHITE PEPPER 17 [hp_X]/1 mL; SAW PALMETTO 3 [hp_X]/1 mL; URTICA URENS 3 [hp_X]/1 mL; POPULUS TREMULOIDES POLLEN 3 [hp_X]/1 mL
INACTIVE INGREDIENTS: SODIUM CHLORIDE; WATER

Berberis Populus

INDICATIONS AND USAGE

Directions: FOR ORAL USE.

DOSAGE AND ADMINISTRATION

Take the contents of one ampule under the tongue and hold for 30 seconds, then swallow.

ACTIVE INGREDIENT

Active Ingredients: Berberis (Barberry) 2X, Populus (Aspen) 3X, Sabal serr. (Dwarf palm) 3X, Urtica urens (Small nettle) 3X, Resina laricis (Larch resin) 8X, Piper (White pepper) 17X

Inactive Ingredients: Water, Salt

PURPOSE

Use: Temporary relief of headache.

KEEP OUT OF REACH OF CHILDREN.

WARNINGS

Warnings: Claims based on traditional homeopathic practice, not accepted medical evidence. Not FDA evaluated. Do not use if allergic to any ingredient. Consult a doctor before use for serious conditions or if conditions worsen or persist. If pregnant or nursing, consult a doctor before use.

Questions? Call 866.642.2858
Made by Uriel, East Troy, WI 53120
www.urielpharmacy.com